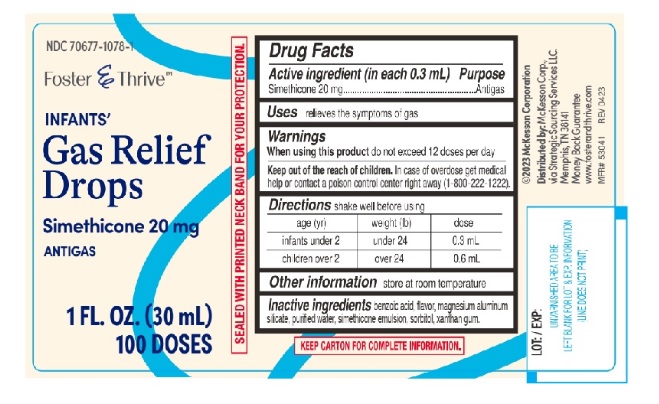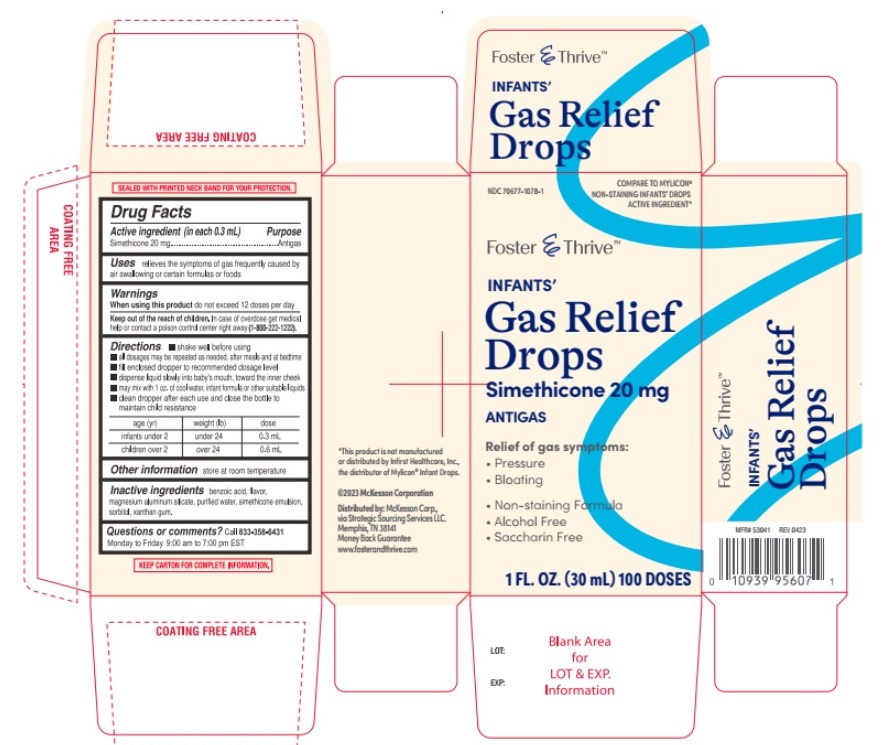 DRUG LABEL: Foster and Thrive infants Gas relief
NDC: 70677-1078 | Form: SOLUTION/ DROPS
Manufacturer: Strategic Sourcing Services LLC
Category: otc | Type: Human OTC Drug Label
Date: 20241213

ACTIVE INGREDIENTS: DIMETHICONE 20 mg/0.3 mL
INACTIVE INGREDIENTS: BENZOIC ACID; Magnesium Aluminum silicate; WATER; SORBITOL; XANTHAN GUM

Foster and Thrive infants Gas relief 520

ACTIVE INGREDIENT(S)

Simethicone 20 mg

PURPOSE

Antigas

USE(S)

relieves the symptoms of gas frequently caused by air swallowing or certain formulas or foods

WARNINGS

.

WHEN USING THIS PRODUCT

do not exceed 12 doses per day

KEEP OUT OF REACH OF CHILDREN.

In case of overdose, get medical help or contact a Poison Control Center right away (1-800-222-1222).

DIRECTIONS

- shake well before using
- all dosages may be repeated as needed, after meals and at bedtime
- fill enclosed dropper to recommended dosage level
- dispense liquid slowly into baby's mouth, toward the inner cheek
- may mix with 1 oz. of cool water, infant formula or other suitable liquids.
- clean dropper after each use and close the bottle to maintain child resistance

age (yr) | weight (lb) | dose
infants under 2 | under 24 | 0.3 mL
children over 2 | over 24 | 0.6 mL

OTHER INFORMATION

store at room temperature

INACTIVE INGRADIENTS

benzoic acid, flavor, magnesium aluminum silicate, purified water, simethicone emulsion, sorbitol, xanthan gum.

QUESTIONS OR COMMENTS?

Call 833-358-6431 Monday to Friday 9:00 to 7:00 pm EST

PRINCIPAL DISPLAY PANEL

NDC 70677-1078-1

COMPARE TO MYLICON® NON-STAINING INFANTS' DROPS

ACTIVE INGREDIENT*

Foster and Thrive TM

INFANTS'

Gas Relief Drops

Simethicone 20 mg

ANTIGAS

Relief of gas symptoms:

- Pressure
- Bloating

- Non-staining Formula
- Alcohol Free
- Saccharin Free

1 FL. OZ. (30 mL) 100 Doses